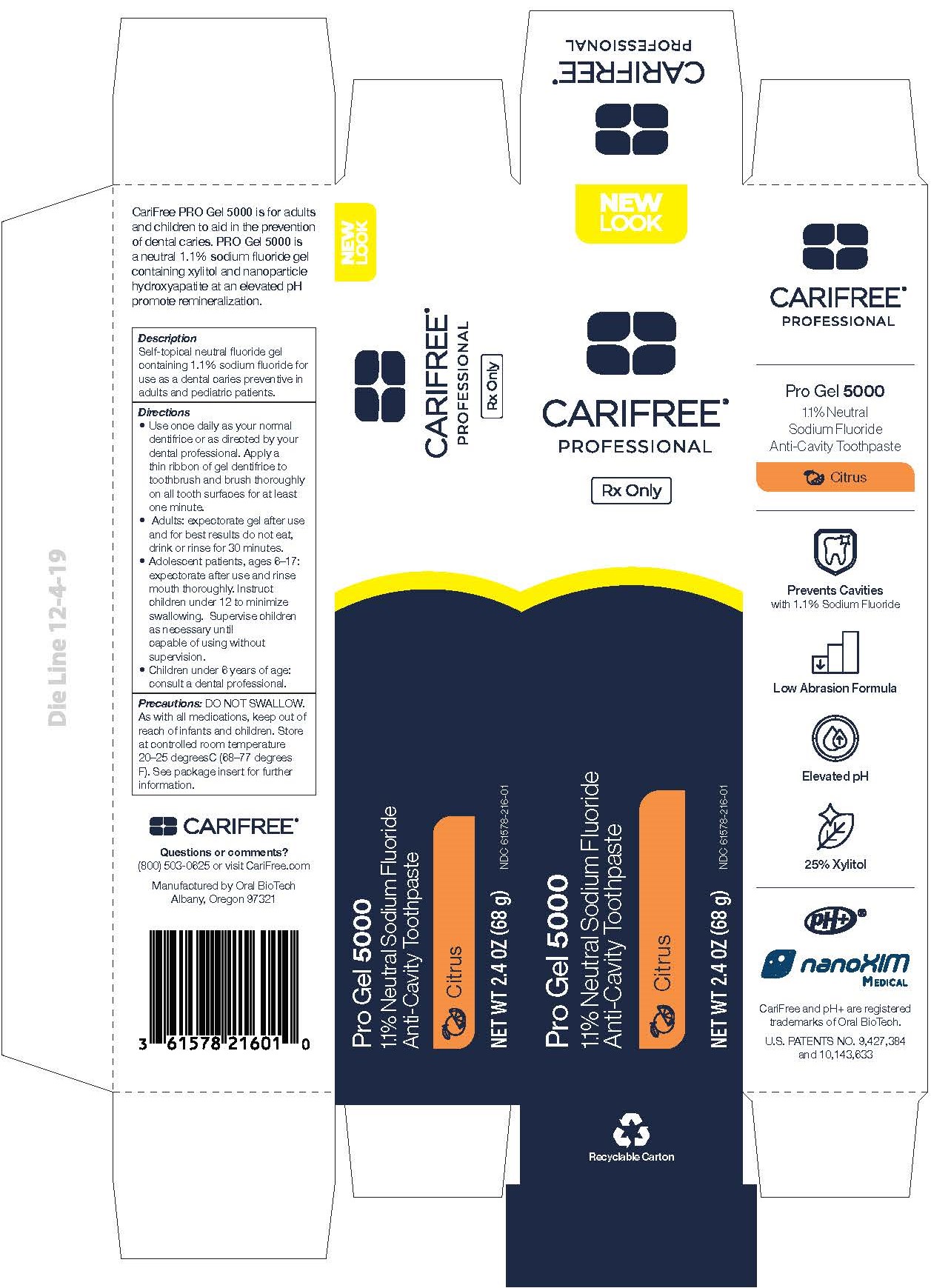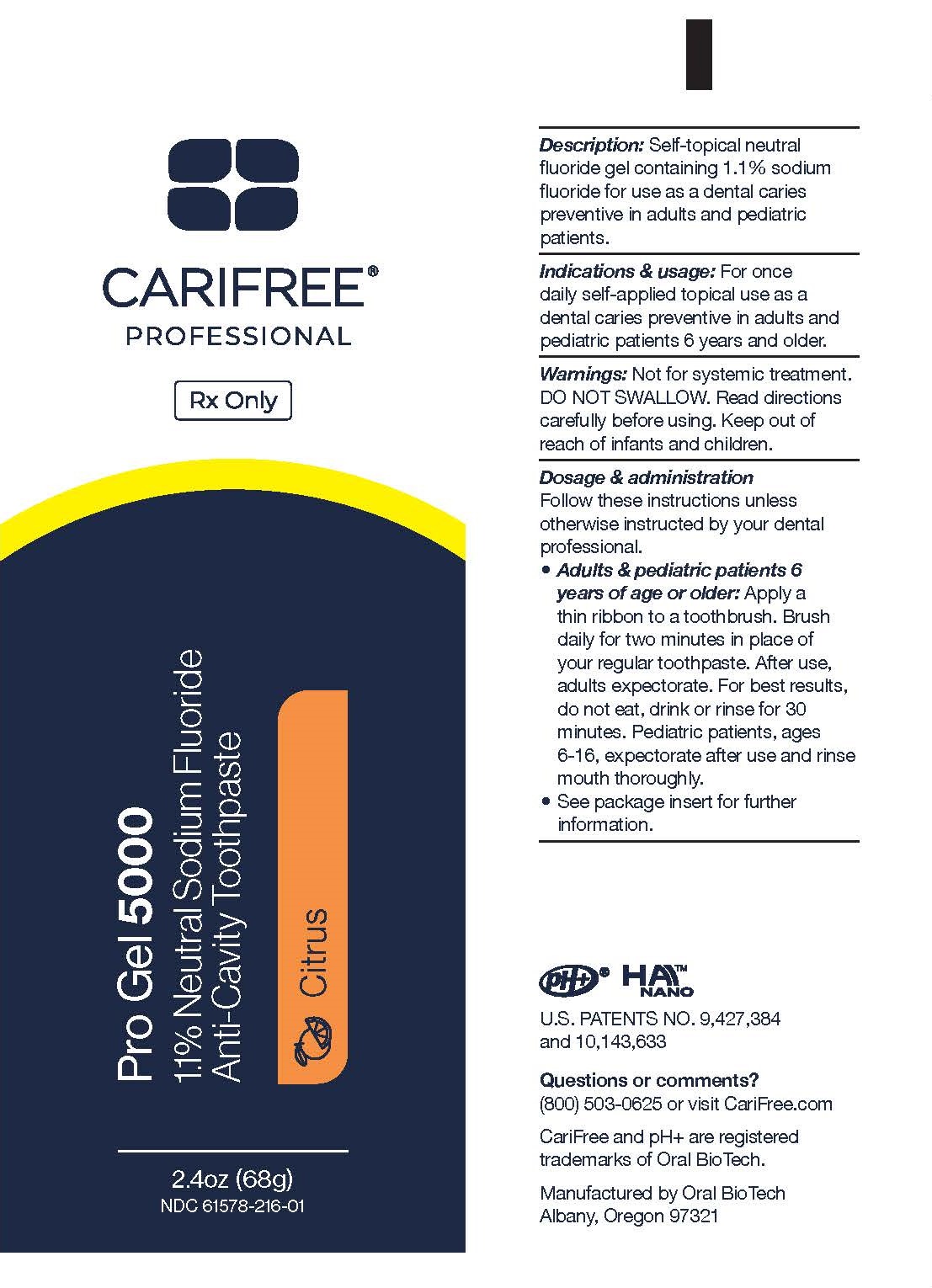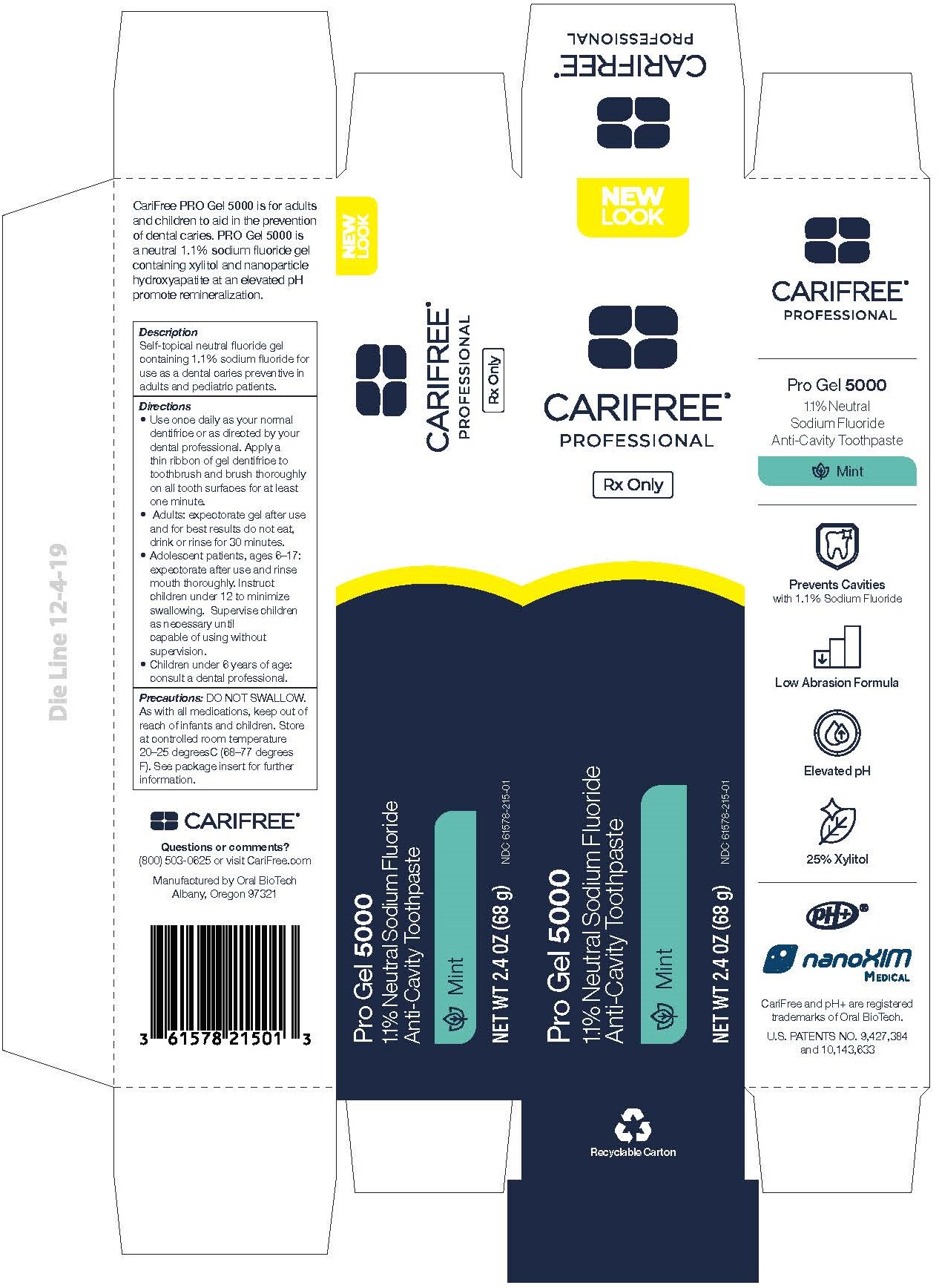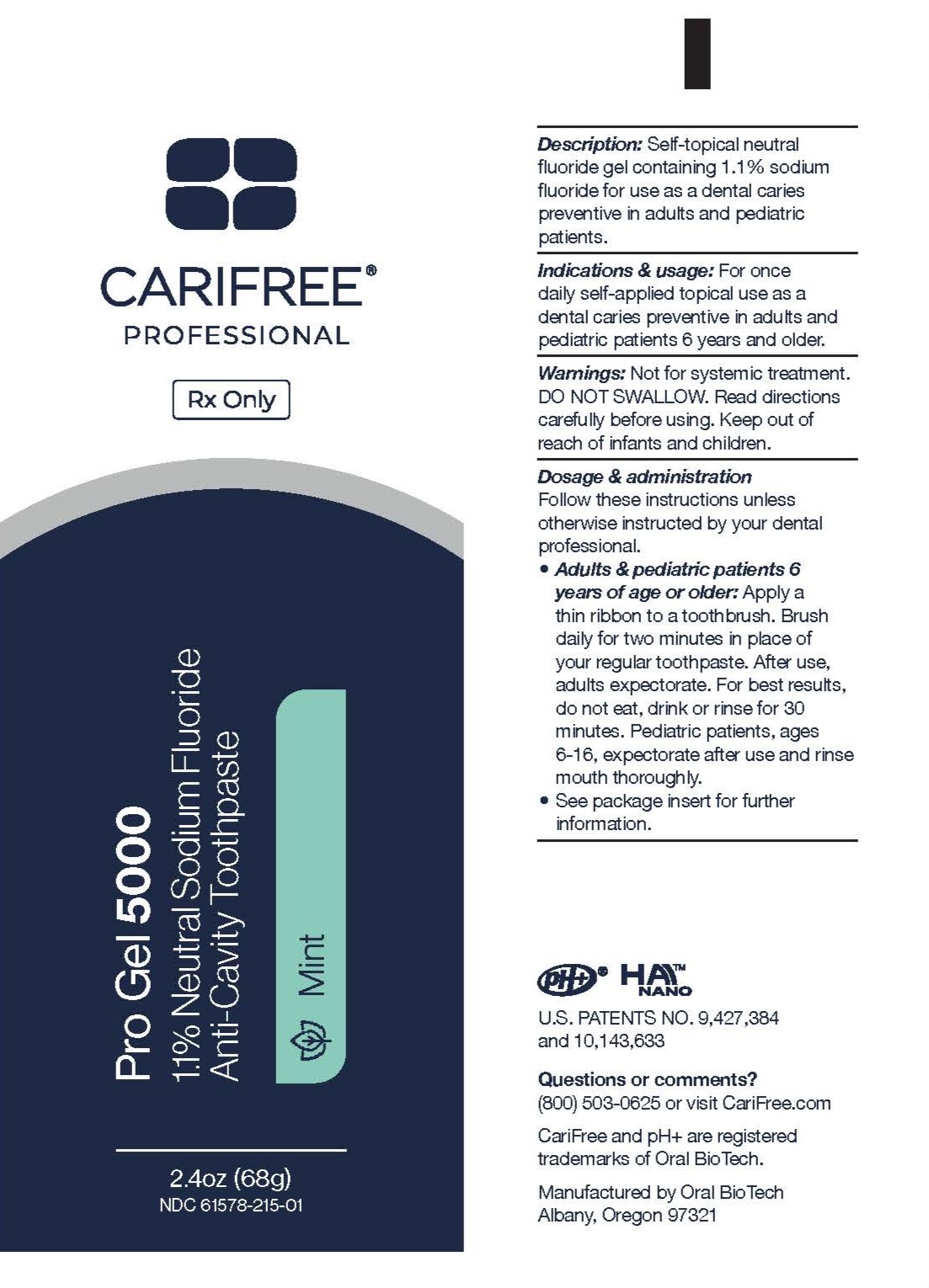 DRUG LABEL: PRO Gel 5000
NDC: 61578-215 | Form: GEL, DENTIFRICE
Manufacturer: DENTAL ALLIANCE HOLDINGS LLC
Category: prescription | Type: HUMAN PRESCRIPTION DRUG LABEL
Date: 20251229

ACTIVE INGREDIENTS: SODIUM FLUORIDE 5000 ug/1 g
INACTIVE INGREDIENTS: GLYCERIN; HYDRATED SILICA; MALTITOL; TRIBASIC CALCIUM PHOSPHATE; HYDROXYETHYL CELLULOSE (3000 CPS AT 1%); MENTHOL; POLYSORBATE 20; POTASSIUM SORBATE; SACCHARIN; SODIUM BENZOATE; SODIUM BICARBONATE; SODIUM HYDROXIDE; SODIUM LAURYL SULFATE; WATER; XYLITOL

Gel 5000

Description:

Self-topical neutral fluoride gel containing 1.1% sodium fluoride for use as a dental caries preventive in adults and pediatric patients.

Active Ingredient:

Sodium Fluoride, 1.1% (w/w)

Other Ingredients:

Glycerin, Hydrated Silica, Hydrogenated Starch Hydrolysate (HSH), Hydroxyapatite, Hydroxyethyl Cellulose, Natural Flavors (Mint only), Natural and Artificial Flavors (Citrus only), Polysorbate 20, Potassium Sorbate, Saccharin, Sodium Benzoate, Sodium Bicarbonate, Sodium Hydroxide, Sodium Lauryl Sulfate, Water, Xylitol

Clinical Pharmacology:

Frequent topical applications to the teeth with preparations having a relatively high fluoride content increase tooth resistance to acid dissolution and enhance penetration of the fluoride ion into the tooth structure.

Indications and Use:

A dental caries preventive; for once daily self-applied topical use. It is well established that a 1.1% sodium fluoride is safe and extraordinarily effective as a caries preventive when applied frequently with mouthpiece applicators.1-4 CariFree CTx4 Gel 5000 brand of 1.1% sodium fluoride toothpaste in a squeeze tube is easily applied onto a toothbrush as well as a mouthpiece tray. This prescription dental gel should be used once daily following use of a regular toothpaste unless otherwise instructed by your dental professional. May be used in areas where drinking water is fluoridated since topical fluoride cannot produce fluorosis. (See Warnings for exception)

Contraindications:

Do not use in pediatric patients under age 6 years unless recommended by a dentist or physician.

Warnings:

Prolonged daily ingestion may result in various degrees of dental fluorosis in pediatric patients under age 6 years, especially if water fluoridation exceeds 0.6 ppm. Use in pediatric patients under age 6 years requires special supervision to prevent repeated swallowing of gel. Read directions carefully before using. Keep out of reach of infants and children.

Precautions:

General: Not for systemic treatments. DO NOT SWALLOW.

Carcinogenesis, Mutagenesis, Impairment of Fertility:

In a study conducted in rodents, no carcinogenesis was found in male and female mice and female rats treated with fluoride at dose levels ranging from 4.1 to 9.1 mg/kg of body weight. Equivocal evidence of carcinogenesis was reported in male rats treated with 2.5 and 4.1 mg/kg of body weight. In a second study, no carcinogenesis was observed in rats, males or females, treated with fluoride up to 11.3 mg/kg of body weight. Epidemiological data provided no credible evidence for an association between fluoride, either naturally occurring or added to drinking water, and risk of human cancer.
Fluoride is not mutagenic in standard bacterial systems. It has been shows that fluoride ion has potential to induce chromosome aberrations in cultured human and rodent cells at doses much higher than those to which humans are exposed. In vivo data are conflicting. Some studies report chromosome damage in rodents, while other studies using similar protocols report negative results.
Potential adverse reproductive effects of fluoride exposure in humans has not been adequately evaluated. Adverse effects on reproduction were reported for rats, mice, fox, and cattle exposed to 100 ppm or greater concentrations of fluoride in their diet or drinking water. Other studies conducted in rats demonstrated that lower concentrations of fluoride (5 mg/kg of body weight) did not result in impaired fertility and reproductive capabilities.

Pregnancy:

Pregnancy Category B. It has been shown that fluoride crosses the placenta of rats, but only 0.01% of the amount administered is incorporated in fetal tissue. Animal studies (rats, mice, rabbits) have shown that fluoride is not teratogen. Maternal exposure to 12.2 mg fluoride/kg of body weight (rats) or 13.1 mg/kg of body weight (rabbits) did not affect the litter size or fetal weight and did not increase the frequency of skeletal or visceral malformations. There are no adequate and well-controlled studies in pregnant women. However, epidemiological studies conducted in areas with high levels of naturally fluoridated water showed no increase in birth defects. Heavy exposure to fluoride during in utero development may result in skeletal fluorosis, which becomes evident in childhood.

Nursing Mothers:

It is not known if fluoride is excreted in human milk. However, many drugs are excreted in milk, and caution should be exercised when products containing fluoride are administered to a nursing woman. Reduce milk production was reported in farm-raised fox when the animals were fed a diet containing a high concentration of fluoride (98-137 mg/kg of body weight). No adverse effects on parturition, lactation, or offspring were seen in rats administered fluoride up to 5 mg/kg of body weight.

Pediatric Use:

The use of CariFree CTx4 Gel 5000 in pediatric age group 6 to 16 years as a caries preventive is supported by pioneering clinical studies with 1.1% sodium fluoride gels in mouth trays in students age 11 to 14 years conducted by Englander et al.2-4 Safety and effectiveness in pediatric patients below the age of 6 years have not been established. Please refer to Contraindications and Warnings sections.

Adverse Reactions:

Allergic reactions and other idiosyncrasies have been rarely reported.

Overdosage:

Accidental ingestion of large amounts of fluoride may result in acute burning in the mouth and sore tongue. Nauseau, vomiting, and diarrhea may occur soon after ingestion (within 30 minutes) and are accompanied by salivation, hematemesis, and epigastric cramping abdominal pain. These symptoms may persist for 24 hours. If less than 5 mg fluoride/kg body weight (ie, less than 2.3 mg fluoride/lb body weight) have been ingested, give calcium (eg, milk) orally to relieve gastrointestinal symptoms and observe for a few hours. If more than 5 mg fluoride/kg body weight (ie, more than 2.3 mg fluoride/lb body weight) have been ingested, induce vomiting, give orally soluble calcium (eg, milk, 5% calcium gluconate or calcium lactate solution) and immediately seek medical assistance. For accidental ingestion of more than 15 mg fluoride/kg of body weight (ie, more than 6.9 mg fluoride/lb body weight), induce vomiting and admit immediately to a hospital facility.
A treatment dose (a thin ribbon) of CariFree CTx4 Gel 5000 contains 2.5 mg fluoride. A 2 oz tube contains 284 mg fluoride.

Dosage and Administration:

Follow these instructions unless otherwise instructed by your dental professional:
1. After brushing with toothpaste, adults and pediatric patients 6 years of age and older, apply a thin ribbon of gel to the teeth with a toothbrush for at least one minute, preferably at bedtime.
2. Adult patients, expectorate gel after use. For best results, do not eat, drink or rinse for 30 minutes. Pediatric patients, age 6-16, expectorate gel after use and rinse mouth thoroughly.

How Supplied:

2 oz (56.699g) tube.

NDC# 61578-205-01 (Mint)

NDC# 61578-206-01 (Citrus)

Storage:

Store at controlled room temperature, 20-25° C (68-77°F)

References:

1. American Dental Association, Accepted Dental Therapeutics, Ed 40, Chicago (1984): 405-407.
2. HR Englander et al, “Clinical Anticaries Effect of Repeated Topical Sodium Fluoride Applications by Mouthpieces,” JADA, 75 (1967): 638-644.
3. HR Englander et al, “Residual Anticaries Effect of Repeated Topical Sodium Fluoride Applications by Mouthpieces,” JADA, 78 (1969): 783-787.
4. HR Englader et al, “Incremental Rates of Dental Caries After Repeated Topical Sodium Fluoride
Applications in Children with Lifelong Consumption of Fluoridated Water,” JADA, 82 (1971): 354-358.

NDC 61578-215-01 Pro Gel Mint Enclosure and Carton Labels

CARIFREE®

PROFESSIONAL

Rx Only

Pro Gel 5000

1.1% Neutral Sodium Fluoride Anti-Cavity Toothpaste

Mint

2.4oz (68g)

NDC 61578-215-01

Description: Self-topical neutral fluoride gel containing 1.1% sodium fluoride for use as a dental caries preventive in adults and pediatric patients.

Indications & usage: For once daily self-applied topical use as a dental caries preventive in adults and pediatric patients 6 years and older.

Warnings: Not for systemic treatment. DO NOT SWALLOW. Read directions carefully before using. Keep out of reach of infants and children.

Dosage & administration

Follow these instructions unless otherwise instructed by your dental professional.

- Adults & pediatric patients 6 years of age or older: Apply a thin ribbon to a toothbrush. Brush daily for two minutes in place of your regular toothpaste. After use, adults expectorate. For best results, do not eat, drink or rinse for 30 minutes. Pediatric patients, ages 6-16, expectorate after use and rinse mouth thoroughly.
- See package insert for further information.

pH+® HAI NANO

U.S. PATENTS NO. 9,427,384 and 10,143,633

Questions or comments?

(800) 503-0625 or visit CariFree.com

CariFree and pH+ are registered trademarks of Oral BioTech.

Manufactured by Oral BioTech

Albany, Oregon 97321

CARIFREE®

PROFESSIONAL

Rx Only

Pro Gel 5000

1.1% Neutral Sodium Fluoride

Anti-Cavity Toothpaste

Mint

NET WT 2.4 OZ (68 g) NDC 61578-215-01

CariFree PRO Gel 5000 is for adults and children to aid in the prevention of dental caries. PRO Gel 5000 is a neutral 1.1% sodium fluoride gel containing xylitol and nanoparticle hydroxyapatite at an elevated pH promote remineralization.

Description

Self-topical neutral fluoride gel containing 1.1% sodium fluoride for use as a dental caries preventive in adults and pediatric patients.

Directions

- Use once daily as your normal dentifrice or as directed by your dental professional. Apply a thin ribbon of gel dentifrice to toothbrush and brush thoroughly on all tooth surfaces for at least one minute.
- Adults: expectorate gel after use and for best results do not eat, drink or rinse for 30 minutes.
- Adolescent patients, ages 6–17: expectorate after use and rinse mouth thoroughly. Instruct children under 12 to minimize swallowing. Supervise children as necessary until capable of using without supervision.
- Children under 6 years of age: consult a dental professional.

Precautions: DO NOT SWALLOW. As with all medications, keep out of reach of infants and children. Store at controlled room temperature 20–25 degreesC (68–77 degreesF). See package insert for further information.

CARIFREE®

Questions or comments?

(800) 503-0625 or visit CariFree.com

Manufactured by Oral BioTech

Albany, Oregon 97321

3 61578 21501 3

Pro Gel 5000

1.1% Neutral Sodium Fluoride Anti-Cavity Toothpaste

Mint

Prevents Cavities

with 1.1% Sodium Fluoride

Low Abrasion Formula

Elevated pH

25% Xylitol

pH+®

nanoXIM Medical

CariFree and pH+ are registered trademarks of Oral BioTech.

U.S. Patents No. 9,427,384 and 10,143,633

NDC 61578-216-01 Pro Gel Citrus Enclosure and Carton Labels

CARIFREE®

PROFESSIONAL

Rx Only

Pro Gel 5000

1.1% Neutral Sodium Fluoride Anti-Cavity Toothpaste

Citrus

2.4oz (68g)

NDC 61578-216-01

Description: Self-topical neutral fluoride gel containing 1.1% sodium fluoride for use as a dental caries preventive in adults and pediatric patients.

Indications & usage: For once daily self-applied topical use as a dental caries preventive in adults and pediatric patients 6 years and older.

Warnings: Not for systemic treatment. DO NOT SWALLOW. Read directions carefully before using. Keep out of reach of infants and children.

Dosage & administration

Follow these instructions unless otherwise instructed by your dental professional.

- Adults & pediatric patients 6 years of age or older: Apply a thin ribbon to a toothbrush. Brush daily for two minutes in place of your regular toothpaste. After use, adults expectorate. For best results, do not eat, drink or rinse for 30 minutes. Pediatric patients, ages 6-16, expectorate after use and rinse mouth thoroughly.
- See package insert for further information.

pH+® HAI NANO

U.S. PATENTS NO. 9,427,384 and 10,143,633

Questions or comments?

(800) 503-0625 or visit CariFree.com

CariFree and pH+ are registered trademarks of Oral BioTech.

Manufactured by Oral BioTech

Albany, Oregon 97321

CARIFREE®

PROFESSIONAL

Rx Only

Pro Gel 5000

1.1% Neutral Sodium Fluoride

Anti-Cavity Toothpaste

Citrus

NET WT 2.4 OZ (68 g) NDC 61578-216-01

CariFree PRO Gel 5000 is for adults and children to aid in the prevention of dental caries. PRO Gel 5000 is a neutral 1.1% sodium fluoride gel containing xylitol and nanoparticle hydroxyapatite at an elevated pH promote remineralization.

Description

Self-topical neutral fluoride gel containing 1.1% sodium fluoride for use as a dental caries preventive in adults and pediatric patients.

Directions

- Use once daily as your normal dentifrice or as directed by your dental professional. Apply a thin ribbon of gel dentifrice to toothbrush and brush thoroughly on all tooth surfaces for at least one minute.
- Adults: expectorate gel after use and for best results do not eat, drink or rinse for 30 minutes.
- Adolescent patients, ages 6–17: expectorate after use and rinse mouth thoroughly. Instruct children under 12 to minimize swallowing. Supervise children as necessary until capable of using without supervision.
- Children under 6 years of age: consult a dental professional.

Precautions: DO NOT SWALLOW. As with all medications, keep out of reach of infants and children. Store at controlled room temperature 20–25 degreesC (68–77 degreesF). See package insert for further information.

CARIFREE®

Questions or comments?

(800) 503-0625 or visit CariFree.com

Manufactured by Oral BioTech

Albany, Oregon 97321

3 61578 21601 3

Pro Gel 5000

1.1% Neutral Sodium Fluoride Anti-Cavity Toothpaste

Citrus

Prevents Cavities

with 1.1% Sodium Fluoride

Low Abrasion Formula

Elevated pH

25% Xylitol

pH+®

nanoXIM Medical

CariFree and pH+ are registered trademarks of Oral BioTech.

U.S. Patents No. 9,427,384 and 10,143,633